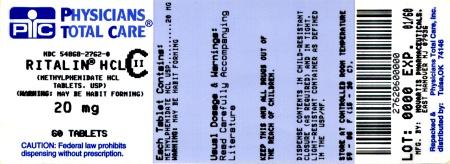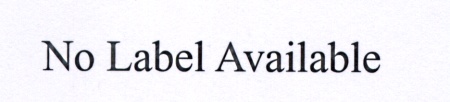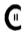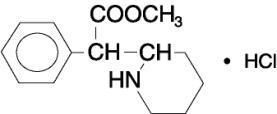 DRUG LABEL: Ritalin
                        
NDC: 54868-1706 | Form: TABLET
Manufacturer: Physicians Total Care, Inc.
Category: prescription | Type: HUMAN PRESCRIPTION DRUG LABEL
Date: 20120120
DEA Schedule: CII

ACTIVE INGREDIENTS: METHYLPHENIDATE HYDROCHLORIDE 5 mg/1 1
INACTIVE INGREDIENTS: D&C YELLOW NO. 10; LACTOSE MONOHYDRATE; MAGNESIUM STEARATE; POLYETHYLENE GLYCOL; SUCROSE; TALC

Ritalin

Ritalin® hydrochloride
methylphenidate hydrochloride
tablets USP

Ritalin-SR®
methylphenidate hydrochloride USP
sustained-release tablets

Rx only

Prescribing Information

DESCRIPTION

Ritalin hydrochloride, methylphenidate hydrochloride USP, is a mild central nervous system (CNS) stimulant, available as tablets of 5, 10, and 20 mg for oral administration; Ritalin-SR is available as sustained-release tablets of 20 mg for oral administration. Methylphenidate hydrochloride is methyl α-phenyl-2-piperidineacetate hydrochloride, and its structural formula is

Methylphenidate hydrochloride USP is a white, odorless, fine crystalline powder. Its solutions are acid to litmus. It is freely soluble in water and in methanol, soluble in alcohol, and slightly soluble in chloroform and in acetone. Its molecular weight is 269.77.

Inactive Ingredients. Ritalin tablets: D&C Yellow No. 10 (5-mg and 20-mg tablets), FD&C Green No. 3 (10-mg tablets), lactose, magnesium stearate, polyethylene glycol, starch (5-mg and 10-mg tablets), sucrose, talc, and tragacanth (20-mg tablets).

Ritalin-SR tablets: Cellulose compounds, cetostearyl alcohol, lactose, magnesium stearate, mineral oil, povidone, titanium dioxide, and zein.

CLINICAL PHARMACOLOGY

Pharmacodynamics

Ritalin is a mild central nervous system stimulant.

The mode of action in man is not completely understood, but Ritalin presumably activates the brain stem arousal system and cortex to produce its stimulant effect.

There is neither specific evidence which clearly establishes the mechanism whereby Ritalin produces its mental and behavioral effects in children, nor conclusive evidence regarding how these effects relate to the condition of the central nervous system.

Effects on QT Interval

The effect of Focalin® XR (dexmethylphenidate, the pharmacologically active d-enantiomer of Ritalin) on the QT interval was evaluated in a double-blind, placebo- and open label active (moxifloxacin)-controlled study following single doses of Focalin® XR 40mg in 75 healthy volunteers. ECGs were collected up to 12 h post-dose. Frederica’s method for heart rate correction was employed to derive the corrected QT interval (QTcF). The maximum mean prolongation of QTcF intervals was <5 ms, and the upper limit of the 90% confidence interval was below 10 ms for all time matched comparisons versus placebo. This was below the threshold of clinical concern and there was no evident-exposure response relationship.

Pharmacokinetics

Ritalin in the SR tablets is more slowly but as extensively absorbed as in the regular tablets. Relative bioavailability of the SR tablet compared to the Ritalin tablet, measured by the urinary excretion of Ritalin major metabolite (α-phenyl-2-piperidine acetic acid) was 105% (49%-168%) in children and 101% (85%-152%) in adults. The time to peak rate in children was 4.7 hours (1.3-8.2 hours) for the SR tablets and 1.9 hours (0.3-4.4 hours) for the tablets. An average of 67% of SR tablet dose was excreted in children as compared to 86% in adults.

In a clinical study involving adult subjects who received SR tablets, plasma concentrations of Ritalin’s major metabolite appeared to be greater in females than in males. No gender differences were observed for Ritalin plasma concentration in the same subjects.

INDICATIONS

Attention Deficit Disorders, Narcolepsy

Attention Deficit Disorders (previously known as Minimal Brain Dysfunction in Children). Other terms being used to describe the behavioral syndrome below include: Hyperkinetic Child Syndrome, Minimal Brain Damage, Minimal Cerebral Dysfunction, Minor Cerebral Dysfunction.

Ritalin is indicated as an integral part of a total treatment program which typically includes other remedial measures (psychological, educational, social) for a stabilizing effect in children with a behavioral syndrome characterized by the following group of developmentally inappropriate symptoms: moderate-to-severe distractibility, short attention span, hyperactivity, emotional lability, and impulsivity. The diagnosis of this syndrome should not be made with finality when these symptoms are only of comparatively recent origin. Nonlocalizing (soft) neurological signs, learning disability, and abnormal EEG may or may not be present, and a diagnosis of central nervous system dysfunction may or may not be warranted.

Special Diagnostic Considerations

Specific etiology of this syndrome is unknown, and there is no single diagnostic test. Adequate diagnosis requires the use not only of medical but of special psychological, educational, and social resources.

Characteristics commonly reported include: chronic history of short attention span, distractibility, emotional lability, impulsivity, and moderate-to-severe hyperactivity; minor neurological signs and abnormal EEG. Learning may or may not be impaired. The diagnosis must be based upon a complete history and evaluation of the child and not solely on the presence of one or more of these characteristics.

Drug treatment is not indicated for all children with this syndrome. Stimulants are not intended for use in the child who exhibits symptoms secondary to environmental factors and/or primary psychiatric disorders, including psychosis. Appropriate educational placement is essential and psychosocial intervention is generally necessary. When remedial measures alone are insufficient, the decision to prescribe stimulant medication will depend upon the physician’s assessment of the chronicity and severity of the child’s symptoms.

CONTRAINDICATIONS

Marked anxiety, tension, and agitation are contraindications to Ritalin, since the drug may aggravate these symptoms. Ritalin is contraindicated also in patients known to be hypersensitive to the drug, in patients with glaucoma, and in patients with motor tics or with a family history or diagnosis of Tourette’s syndrome.

Ritalin is contraindicated during treatment with monoamine oxidase inhibitors, and also within a minimum of 14 days following discontinuation of a monoamine oxidase inhibitor (hypertensive crises may result).

WARNINGS

Serious Cardiovascular Events

Sudden Death and Pre-Existing Structural Cardiac Abnormalities or Other Serious Heart Problems

Children and Adolescents

Sudden death has been reported in association with CNS stimulant treatment at usual doses in children and adolescents with structural cardiac abnormalities or other serious heart problems. Although some serious heart problems alone carry an increased risk of sudden death, stimulant products generally should not be used in children or adolescents with known serious structural cardiac abnormalities, cardiomyopathy, serious heart rhythm abnormalities, or other serious cardiac problems that may place them at increased vulnerability to the sympathomimetic effects of a stimulant drug.

Adults

Sudden death, stroke, and myocardial infarction have been reported in adults taking stimulant drugs at usual doses for ADHD. Although the role of stimulants in these adult cases is also unknown, adults have a greater likelihood than children of having serious structural cardiac abnormalities, cardiomyopathy, serious heart rhythm abnormalities, coronary artery disease, or other serious cardiac problems. Adults with such abnormalities should also generally not be treated with stimulant drugs.

Hypertension and Other Cardiovascular Conditions

Stimulant medications cause a modest increase in average blood pressure (about 2-4 mmHg) and average heart rate (about 3-6 bpm), and individuals may have larger increases. While the mean changes alone would not be expected to have short-term consequences, all patients should be monitored for larger changes in heart rate and blood pressure. Caution is indicated in treating patients whose underlying medical conditions might be compromised by increases in blood pressure or heart rate, e.g., those with pre-existing hypertension, heart failure, recent myocardial infarction, or ventricular arrhythmia.

Assessing Cardiovascular Status in Patients being Treated with Stimulant Medications

Children, adolescents, or adults who are being considered for treatment with stimulant medications should have a careful history (including assessment for a family history of sudden death or ventricular arrhythmia) and physical exam to assess for the presence of cardiac disease, and should receive further cardiac evaluation if findings suggest such disease (e.g., electrocardiogram and echocardiogram). Patients who develop symptoms such as exertional chest pain, unexplained syncope, or other symptoms suggestive of cardiac disease during stimulant treatment should undergo a prompt cardiac evaluation.

Psychiatric Adverse Events

Pre-Existing Psychosis

Administration of stimulants may exacerbate symptoms of behavior disturbance and thought disorder in patients with a pre-existing psychotic disorder.

Bipolar Illness

Particular care should be taken in using stimulants to treat ADHD in patients with comorbid bipolar disorder because of concern for possible induction of a mixed/ manic episode in such patients. Prior to initiating treatment with a stimulant, patients with comorbid depressive symptoms should be adequately screened to determine if they are at risk for bipolar disorder; such screening should include a detailed psychiatric history, including a family history of suicide, bipolar disorder, and depression.

Emergence of New Psychotic or Manic Symptoms

Treatment emergent psychotic or manic symptoms, e. g., hallucinations, delusional thinking, or mania in children and adolescents without a prior history of psychotic illness or mania can be caused by stimulants at usual doses. If such symptoms occur, consideration should be given to a possible causal role of the stimulant, and discontinuation of treatment may be appropriate. In a pooled analysis of multiple short-term, placebo-controlled studies, such symptoms occurred in about 0.1% (4 patients with events out of 3,482 exposed to methylphenidate or amphetamine for several weeks at usual doses) of stimulant-treated patients compared to 0 in placebo-treated patients.

Aggression

Aggressive behavior or hostility is often observed in children and adolescents with ADHD, and has been reported in clinical trials and the postmarketing experience of some medications indicated for the treatment of ADHD. Although there is no systematic evidence that stimulants cause aggressive behavior or hostility, patients beginning treatment for ADHD should be monitored for the appearance of or worsening of aggressive behavior or hostility.

Long-Term Suppression of Growth

Careful follow-up of weight and height in children ages 7 to 10 years who were randomized to either methylphenidate or non-medication treatment groups over 14 months, as well as in naturalistic subgroups of newly methylphenidate-treated and non-medication treated children over 36 months (to the ages of 10 to 13 years), suggests that consistently medicated children (i.e., treatment for 7 days per week throughout the year) have a temporary slowing in growth rate (on average, a total of about 2 cm less growth in height and 2.7 kg less growth in weight over 3 years), without evidence of growth rebound during this period of development. Published data are inadequate to determine whether chronic use of amphetamines may cause a similar suppression of growth, however, it is anticipated that they likely have this effect as well. Therefore, growth should be monitored during treatment with stimulants, and patients who are not growing or gaining height or weight as expected may need to have their treatment interrupted.

Seizures

There is some clinical evidence that stimulants may lower the convulsive threshold in patients with prior history of seizures, in patients with prior EEG abnormalities in absence of seizures, and, very rarely, in patients without a history of seizures and no prior EEG evidence of seizures. In the presence of seizures, the drug should be discontinued.

Visual Disturbance

Difficulties with accommodation and blurring of vision have been reported with stimulant treatment.

Use in Children Under Six Years of Age

Ritalin should not be used in children under 6 years, since safety and efficacy in this age group have not been established.

Drug Dependence

Ritalin should be given cautiously to patients with a history of drug dependence or alcoholism. Chronic abusive use can lead to marked tolerance and psychological dependence with varying degrees of abnormal behavior. Frank psychotic episodes can occur, especially with parenteral abuse. Careful supervision is required during withdrawal from abusive use, since severe depression may occur. Withdrawal following chronic therapeutic use may unmask symptoms of the underlying disorder that may require follow-up.

PRECAUTIONS

Patients with an element of agitation may react adversely; discontinue therapy if necessary.

Periodic CBC, differential, and platelet counts are advised during prolonged therapy.

Drug treatment is not indicated in all cases of this behavioral syndrome and should be considered only in light of the complete history and evaluation of the child. The decision to prescribe Ritalin should depend on the physician’s assessment of the chronicity and severity of the child’s symptoms and their appropriateness for his/her age. Prescription should not depend solely on the presence of one or more of the behavioral characteristics.

When these symptoms are associated with acute stress reactions, treatment with Ritalin is usually not indicated.

Information for Patients

Prescribers or other health professionals should inform patients, their families, and their caregivers about the benefits and risks associated with treatment with methylphenidate and should counsel them in its appropriate use. A patient Medication Guide is available for Ritalin and Ritalin-SR. The prescriber or health professional should instruct patients, their families, and their caregivers to read the Medication Guide and should assist them in understanding its contents. Patients should be given the opportunity to discuss the contents of the Medication Guide and to obtain answers to any questions they may have. The complete text of the Medication Guide is reprinted at the end of this document.

Drug Interactions

Ritalin should not be used in patients being treated (currently or within the proceeding two weeks) with MAO Inhibitors (see CONTRAINDICATIONS, Monoamine Oxidase Inhibitors). Because of possible effects on blood pressure, Ritalin should be used cautiously with pressor agents.

Methylphenidate may decrease the effectiveness of drugs used to treat hypertension. Methylphenidate is metabolized primarily to ritalinic acid by de-esterification and not through oxidative pathways.

Human pharmacologic studies have shown that racemic methylphenidate may inhibit the metabolism of coumarin anticoagulants, anticonvulsants (e.g., phenobarbital, phenytoin, primidone), and tricyclic drugs (e.g., imipramine, clomipramine, desipramine). Downward dose adjustments of these drugs may be required when given concomitantly with methylphenidate. It may be necessary to adjust the dosage and monitor plasma drug concentration (or, in case of coumarin, coagulation times), when initiating or discontinuing methylphenidate.

Carcinogenesis/Mutagenesis/Impairment of Fertility

In a lifetime carcinogenicity study carried out in B6C3F1 mice, methylphenidate caused an increase in hepatocellular adenomas and, in males only, an increase in hepatoblastomas, at a daily dose of approximately 60 mg/kg/day. This dose is approximately 30 times and 4 times the maximum recommended human dose on a mg/kg and mg/m^2 basis, respectively. Hepatoblastoma is a relatively rare rodent malignant tumor type. There was no increase in total malignant hepatic tumors. The mouse strain used is sensitive to the development of hepatic tumors, and the significance of these results to humans is unknown.

Methylphenidate did not cause any increases in tumors in a lifetime carcinogenicity study carried out in F344 rats; the highest dose used was approximately 45 mg/kg/day, which is approximately 22 times and 5 times the maximum recommended human dose on a mg/kg and mg/m^2 basis, respectively.

In a 24-week carcinogenicity study in the transgenic mouse strain p53+/-, which is sensitive to genotoxic carcinogens, there was no evidence of carcinogenicity. Male and female mice were fed diets containing the same concentration of methylphenidate as in the lifetime carcinogenicity study; the high-dose groups were exposed to 60-74 mg/kg/day of methylphenidate.

Methylphenidate was not mutagenic in the in vitro Ames reverse mutation assay or in the in vitro mouse lymphoma cell forward mutation assay. Sister chromatid exchanges and chromosome aberrations were increased, indicative of a weak clastogenic response, in an in vitro assay in cultured Chinese Hamster Ovary (CHO) cells. Methylphenidate was negative in vivo in males and females in the mouse bone marrow micronucleus assay.

Methlyphenidate did not impair fertility in male or female mice that were fed diets containing the drug in an 18-week Continuous Breeding study. The study was conducted at doses up to 160 mg/kg/day, approximately 80-fold and 8-fold the highest recommended dose on a mg/kg and mg/m^2 basis, respectively.

PREGNANCY

Pregnancy Category C

In studies conducted in rats and rabbits, methylphenidate was administered orally at doses of up to 75 and 200 mg/kg/day, respectively, during the period of organogenesis. Teratogenic effects (increased incidence of fetal spina bifida) were observed in rabbits at the highest dose, which is approximately 40 times the maximum recommended human dose (MRHD) on a mg/m^2 basis. The no effect level for embryo-fetal development in rabbits was 60 mg/kg/day (11 times the MRHD on a mg/m^2 basis). There was no evidence of specific teratogenic activity in rats, although increased incidences of fetal skeletal variations were seen at the highest dose level (7 times the MRHD on a mg/m^2 basis), which was also maternally toxic. The no effect level for embryo-fetal development in rats was 25 mg/kg/day (2 times the MRHD on a mg/m^2 basis). When methylphenidate was administered to rats throughout pregnancy and lactation at doses of up to 45 mg/kg/day, offspring body weight gain was decreased at the highest dose (4 times the MRHD on a mg/m^2 basis), but no other effects on postnatal development were observed. The no effect level for pre- and postnatal development in rats was 15 mg/kg/day (equal to the MRHD on a mg/m^2 basis).

Adequate and well-controlled studies in pregnant women have not been conducted. Ritalin should be used during pregnancy only if the potential benefit justifies the potential risk to the fetus.

Nursing Mothers

It is not known whether methylphenidate is excreted in human milk. Because many drugs are excreted in human milk, caution should be exercised if Ritalin is administered to a nursing woman.

Pediatric Use

Ritalin should not be used in children under six years of age (see WARNINGS).

In a study conducted in young rats, methylphenidate was administered orally at doses of up to 100 mg/kg/day for 9 weeks, starting early in the postnatal period (Postnatal Day 7) and continuing through sexual maturity (Postnatal Week 10). When these animals were tested as adults (Postnatal Weeks 13-14), decreased spontaneous locomotor activity was observed in males and females previously treated with 50 mg/kg/day (approximately 6 times the maximum recommended human dose [MRHD] on a mg/m^2 basis) or greater, and a deficit in the acquisition of a specific learning task was seen in females exposed to the highest dose (12 times the MRHD on a mg/m^2 basis). The no effect level for juvenile neurobehavioral development in rats was 5 mg/kg/day (half the MRHD on a mg/m^2 basis). The clinical significance of the long-term behavioral effects observed in rats is unknown.

ADVERSE REACTIONS

Nervousness and insomnia are the most common adverse reactions but are usually controlled by reducing dosage and omitting the drug in the afternoon or evening. Other reactions include hypersensitivity (including skin rash, urticaria, fever, arthralgia, exfoliative dermatitis, erythema multiforme with histopathological findings of necrotizing vasculitis, and thrombocytopenic purpura); anorexia; nausea; dizziness; palpitations; headache; dyskinesia; drowsiness; blood pressure and pulse changes, both up and down; tachycardia; angina; cardiac arrhythmia; abdominal pain; weight loss during prolonged therapy. There have been rare reports of Tourette’s syndrome. Toxic psychosis has been reported. Although a definite causal relationship has not been established, the following have been reported in patients taking this drug: instances of abnormal liver function, ranging from transaminase elevation to hepatic coma; isolated cases of cerebral arteritis and/or occlusion; leukopenia and/or anemia; transient depressed mood; aggressive behavior; a few instances of scalp hair loss. Very rare reports of neuroleptic malignant syndrome (NMS) have been received, and, in most of these, patients were concurrently receiving therapies associated with NMS. In a single report, a ten-year-old boy who had been taking methylphenidate for approximately 18 months experienced an NMS-like event within 45 minutes of ingesting his first dose of venlafaxine. It is uncertain whether this case represented a drug-drug interaction, a response to either drug alone, or some other cause.

In children, loss of appetite, abdominal pain, weight loss during prolonged therapy, insomnia, and tachycardia may occur more frequently; however, any of the other adverse reactions listed above may also occur.

DOSAGE AND ADMINISTRATION

Dosage should be individualized according to the needs and responses of the patient.

Adults

Tablets: Administer in divided doses 2 or 3 times daily, preferably 30 to 45 minutes before meals. Average dosage is 20 to 30 mg daily. Some patients may require 40 to 60 mg daily. In others, 10 to 15 mg daily will be adequate. Patients who are unable to sleep if medication is taken late in the day should take the last dose before 6 p.m.

SR Tablets: Ritalin-SR tablets have a duration of action of approximately 8 hours. Therefore, Ritalin-SR tablets may be used in place of Ritalin tablets when the 8-hour dosage of Ritalin-SR corresponds to the titrated 8-hour dosage of Ritalin. Ritalin-SR tablets must be swallowed whole and never crushed or chewed.

Children (6 years and over)

Ritalin should be initiated in small doses, with gradual weekly increments. Daily dosage above 60 mg is not recommended.

If improvement is not observed after appropriate dosage adjustment over a one-month period, the drug should be discontinued.

Tablets: Start with 5 mg twice daily (before breakfast and lunch) with gradual increments of 5 to 10 mg weekly.

SR Tablets: Ritalin-SR tablets have a duration of action of approximately 8 hours. Therefore, Ritalin-SR tablets may be used in place of Ritalin tablets when the 8-hour dosage of Ritalin-SR corresponds to the titrated 8-hour dosage of Ritalin. Ritalin-SR tablets must be swallowed whole and never crushed or chewed.

If paradoxical aggravation of symptoms or other adverse effects occur, reduce dosage, or, if necessary, discontinue the drug.

Ritalin should be periodically discontinued to assess the child’s condition. Improvement may be sustained when the drug is either temporarily or permanently discontinued.

Drug treatment should not and need not be indefinite and usually may be discontinued after puberty.

OVERDOSAGE

Signs and symptoms of acute overdosage, resulting principally from overstimulation of the central nervous system and from excessive sympathomimetic effects, may include the following: vomiting, agitation, tremors, hyperreflexia, muscle twitching, convulsions (may be followed by coma), euphoria, confusion, hallucinations, delirium, sweating, flushing, headache, hyperpyrexia, tachycardia, palpitations, cardiac arrhythmias, hypertension, mydriasis, and dryness of mucous membranes.

Consult with a Certified Poison Control Center regarding treatment for up-to-date guidance and advice.

Treatment consists of appropriate supportive measures. The patient must be protected against self-injury and against external stimuli that would aggravate overstimulation already present. Gastric contents may be evacuated by gastric lavage. In the presence of severe intoxication, use a carefully titrated dosage of a short-acting barbiturate before performing gastric lavage. Other measures to detoxify the gut include administration of activated charcoal and a cathartic.

Intensive care must be provided to maintain adequate circulation and respiratory exchange; external cooling procedures may be required for hyperpyrexia.

Efficacy of peritoneal dialysis or extracorporeal hemodialysis for Ritalin overdosage has not been established.

HOW SUPPLIED

Tablets 5 mg - round, yellow (imprinted CIBA 7)

Bottles of 20 | NDC 54868-1706-2
Bottles of 60 | NDC 54868-1706-1
Bottles of 100 | NDC 54868-1706-0
Bottles of 120 | NDC 54868-1706-3

Tablets 20 mg - round, pale yellow (imprinted CIBA 34)

Bottles of 60 | NDC 54868-2762-0

Store at 25°C (77°F); excursions permitted to 15-30°C (59-86°F) [see USP Controlled Room Temperature]. Protect from light.

Dispense in tight, light-resistant container (USP).

MEDICATION GUIDE

RITALIN®

(methylphenidate hydrochloride tablets, USP) CII

Read the Medication Guide that comes with RITALIN® before you or your child starts taking it and each time you get a refill. There may be new information. This Medication Guide does not take the place of talking to your doctor about your or your child’s treatment with RITALIN®.

What is the most important information I should know about RITALIN®?
The following have been reported with use of methylphenidate hydrochloride and other stimulant medicines.
1. Heart-related problems:

- sudden death in patients who have heart problems or heart defects
- stroke and heart attack in adults
- increased blood pressure and heart rate

Tell your doctor if you or your child have any heart problems, heart defects, high blood pressure, or a family history of these problems.
Your doctor should check you or your child carefully for heart problems before starting RITALIN®.
Your doctor should check your or your child’s blood pressure and heart rate regularly during treatment with RITALIN®.
Call your doctor right away if you or your child has any signs of heart problems such as chest pain, shortness of breath, or fainting while taking RITALIN®.
2. Mental (Psychiatric) problems:
All Patients

- new or worse behavior and thought problems
- new or worse bipolar illness
- new or worse aggressive behavior or hostility

Children and Teenagers

- new psychotic symptoms (such as hearing voices, believing things that are not true, are suspicious) or new manic symptoms

Tell your doctor about any mental problems you or your child have, or about a family history of suicide, bipolar illness, or depression.
Call your doctor right away if you or your child have any new or worsening mental symptoms or problems while taking RITALIN®, especially seeing or hearing things that are not real, believing things that are not real, or are suspicious.

What Is RITALIN®?

RITALIN® is a central nervous system stimulant prescription medicine. It is used for the treatment of Attention-Deficit Hyperactivity Disorder (ADHD). RITALIN® may help increase attention and decrease impulsiveness and hyperactivity in patients with ADHD.

RITALIN® should be used as a part of a total treatment program for ADHD that may include counseling or other therapies.

RITALIN® is also used in the treatment of a sleep disorder called narcolepsy.

RITALIN® is a federally controlled substance (CII) because it can be abused or lead to dependence. Keep RITALIN® in a safe place to prevent misuse and abuse. Selling or giving away RITALIN® may harm others, and is against the law.
Tell your doctor if you or your child have (or have a family history of) ever abused or been dependent on alcohol, prescription medicines or street drugs.

Who should not take RITALIN®?

RITALIN® should not be taken if you or your child:

- are very anxious, tense, or agitated
- have an eye problem called glaucoma
- have tics or Tourette’s syndrome, or a family history of Tourette’s syndrome. Tics are hard to control repeated movements or sounds.
- are taking or have taken within the past 14 days an anti-depression medicine called a monoamine oxidase inhibitor or MAOI.
- are allergic to anything in RITALIN®. See the end of this Medication Guide for a complete list of ingredients.

RITALIN® should not be used in children less than 6 years old because it has not been studied in this age group.

RITALIN® may not be right for you or your child. Before starting RITALIN® tell your or your child’s doctor about all health conditions (or a family history of) including:

- heart problems, heart defects, high blood pressure
- mental problems including psychosis, mania, bipolar illness, or depression
- tics or Tourette’s syndrome
- seizures or have had an abnormal brain wave test (EEG)

Tell your doctor if you or your child is pregnant, planning to become pregnant, or breast-feeding.

Can RITALIN® be taken with other medicines?

Tell your doctor about all of the medicines that you or your child take including prescription and nonprescription medicines, vitamins, and herbal supplements. RITALIN® and some medicines may interact with each other and cause serious side effects. Sometimes the doses of other medicines will need to be adjusted while taking RITALIN®.

Your doctor will decide whether RITALIN® can be taken with other medicines.

Especially tell your doctor if you or your child takes:

- anti-depression medicines including MAOIs
- seizure medicines
- blood thinner medicines
- blood pressure medicines
- cold or allergy medicines that contain decongestants

Know the medicines that you or your child takes. Keep a list of your medicines with you to show your doctor and pharmacist.

Do not start any new medicine while taking RITALIN® without talking to your doctor first.

How should RITALIN® be taken?

- Take RITALIN® exactly as prescribed. Your doctor may adjust the dose until it is right for you or your child.
- Ritalin is usually taken 2 to 3 times a day.
- Take RITALIN® 30 to 45 minutes before a meal.
- From time to time, your doctor may stop RITALIN® treatment for a while to check ADHD symptoms.
- Your doctor may do regular checks of the blood, heart, and blood pressure while taking RITALIN®. Children should have their height and weight checked often while taking RITALIN®. RITALIN® treatment may be stopped if a problem is found during these check-ups.
- If you or your child takes too much RITALIN® or overdoses, call your doctor or poison control center right away, or get emergency treatment.

What are possible side effects of RITALIN®?

See “What is the most important information I should know about RITALIN®?” for information on reported heart and mental problems.

Other serious side effects include:

- slowing of growth (height and weight) in children
- seizures, mainly in patients with a history of seizures
- eyesight changes or blurred vision

Common side effects include:

- headache • decreased appetite
- stomach ache • nervousness
- trouble sleeping
- nausea

Talk to your doctor if you or your child has side effects that are bothersome or do not go away.

This is not a complete list of possible side effects. Ask your doctor or pharmacist for more information.

How should I store RITALIN®?

- Store RITALIN in a safe place at room temperature, 59 to 86° F (15 to 30° C). Protect from light.
- Keep RITALIN® and all medicines out of the reach of children.

General information about RITALIN®

Medicines are sometimes prescribed for purposes other than those listed in a Medication Guide. Do not use RITALIN® for a condition for which it was not prescribed. Do not give RITALIN® to other people, even if they have the same condition. It may harm them and it is against the law.

This Medication Guide summarizes the most important information about RITALIN®. If you would like more information, talk with your doctor. You can ask your doctor or pharmacist for information about RITALIN® that was written for healthcare professionals. For more information about RITALIN® call 1-888-669-6682.

What are the ingredients in RITALIN®?

Active Ingredient: methylphenidate HCL

Inactive Ingredients: D&C Yellow No.10 (5-mg and 20-mg tablets), FD&C Green No.3 (10-mg tablets), lactose, magnesium stearate, polyethylene glycol, starch (5-mg and 10-mg tablets), sucrose, talc, and tragacanth (20-mg tablets).

Call your doctor for medical advice about side effects. You may report side effects to FDA at 1-800-FDA-1088.

This Medication Guide has been approved by the U.S. Food and Drug Administration.

MEDICATION GUIDE

RITALIN-SR®

(methylphenidate hydrochloride, USP) sustained-release tablets CII

Read the Medication Guide that comes with RITALIN-SR® before you or your child starts taking it and each time you get a refill. There may be new information. This Medication Guide does not take the place of talking to your doctor about your or your child’s treatment with RITALIN-SR®.

What is the most important information I should know about RITALIN-SR®?
The following have been reported with use of methylphenidate hydrochloride and other stimulant medicines.
1. Heart-related problems:

- sudden death in patients who have heart problems or heart defects
- stroke and heart attack in adults
- increased blood pressure and heart rate

Tell your doctor if you or your child have any heart problems, heart defects, high blood pressure, or a family history of these problems.
Your doctor should check you or your child carefully for heart problems before starting RITALIN-SR®.
Your doctor should check your or your child’s blood pressure and heart rate regularly during treatment with RITALIN-SR®.
Call your doctor right away if you or your child has any signs of heart problems such as chest pain, shortness of breath, or fainting while taking RITALIN-SR®.
2. Mental (Psychiatric) problems:
All Patients

- new or worse behavior and thought problems
- new or worse bipolar illness
- new or worse aggressive behavior or hostility

Children and Teenagers

- new psychotic symptoms (such as hearing voices, believing things that are not true, are suspicious) or new manic symptoms

Tell your doctor about any mental problems you or your child have, or about a family history of suicide, bipolar illness, or depression.
Call your doctor right away if you or your child have any new or worsening mental symptoms or problems while taking RITALIN-SR®, especially seeing or hearing things that are not real, believing things that are not real, or are suspicious.

What Is RITALIN-SR®?

RITALIN-SR® is a central nervous system stimulant prescription medicine. It is used for the treatment of Attention-Deficit Hyperactivity Disorder (ADHD). RITALIN-SR® may help increase attention and decrease impulsiveness and hyperactivity in patients with ADHD.

RITALIN-SR® should be used as a part of a total treatment program for ADHD that may include counseling or other therapies.

RITALIN-SR® is also used in the treatment of a sleep disorder called narcolepsy.

RITALIN-SR® is a federally controlled substance (CII) because it can be abused or lead to dependence. Keep RITALIN-SR® in a safe place to prevent misuse and abuse. Selling or giving away RITALIN-SR® may harm others, and is against the law.
Tell your doctor if you or your child have (or have a family history of) ever abused or been dependent on alcohol, prescription medicines or street drugs.

Who should not take RITALIN-SR®?

RITALIN-SR® should not be taken if you or your child:

- are very anxious, tense, or agitated
- have an eye problem called glaucoma
- have tics or Tourette’s syndrome, or a family history of Tourette’s syndrome. Tics are hard to control repeated movements or sounds.
- are taking or have taken within the past 14 days an anti-depression medicine called a monoamine oxidase inhibitor or MAOI.
- are allergic to anything in RITALIN-SR®. See the end of this Medication Guide for a complete list of ingredients.

RITALIN-SR® should not be used in children less than 6 years old because it has not been studied in this age group.

RITALIN-SR® may not be right for you or your child. Before starting RITALIN-SR® tell your or your child’s doctor about all health conditions (or a family history of) including:

- heart problems, heart defects, high blood pressure
- mental problems including psychosis, mania, bipolar illness, or depression
- tics or Tourette’s syndrome
- seizures or have had an abnormal brain wave test (EEG)

Tell your doctor if you or your child is pregnant, planning to become pregnant, or breast-feeding.

Can RITALIN-SR® be taken with other medicines?

Tell your doctor about all of the medicines that you or your child take including prescription and nonprescription medicines, vitamins, and herbal supplements. RITALIN-SR® and some medicines may interact with each other and cause serious side effects. Sometimes the doses of other medicines will need to be adjusted while taking RITALIN-SR®.

Your doctor will decide whether RITALIN-SR® can be taken with other medicines.

Especially tell your doctor if you or your child takes:

- anti-depression medicines including MAOIs
- seizure medicines
- blood thinner medicines
- blood pressure medicines
- cold or allergy medicines that contain decongestants

Know the medicines that you or your child takes. Keep a list of your medicines with you to show your doctor and pharmacist.

Do not start any new medicine while taking RITALIN-SR® without talking to your doctor first.

How should RITALIN-SR® be taken?

- Take RITALIN-SR® exactly as prescribed. Your doctor may adjust the dose until it is right for you or your child.
- Take RITALIN-SR® 30 to 45 minutes before a meal. The effect of a dose of RITALIN-SR usually lasts about 8 hours.
- Do not chew or crush RITALIN-SR® tablets. Swallow RITALIN-SR® tablets whole with water or other liquids. Tell your doctor if you or your child cannot swallow RITALIN-SR® whole. A different medicine may need to be prescribed.
- From time to time, your doctor may stop RITALIN-SR® treatment for a while to check ADHD symptoms.
- Your doctor may do regular checks of the blood, heart, and blood pressure while taking RITALIN-SR®. Children should have their height and weight checked often while taking RITALIN-SR®. RITALIN-SR® treatment may be stopped if a problem is found during these check-ups.
- If you or your child takes too much RITALIN-SR® or overdoses, call your doctor or poison control center right away, or get emergency treatment.

What are possible side effects of RITALIN-SR®?

See “What is the most important information I should know about RITALIN-SR®?” for information on reported heart and mental problems.

Other serious side effects include:

- slowing of growth (height and weight) in children
- seizures, mainly in patients with a history of seizures
- eyesight changes or blurred vision

Common side effects include:

- headache • decreased appetite
- stomach ache • nervousness
- trouble sleeping
- nausea

Talk to your doctor if you or your child has side effects that are bothersome or do not go away.

This is not a complete list of possible side effects. Ask your doctor or pharmacist for more information.

How should I store RITALIN-SR®?

- Store RITALIN-SR® in a safe place at room temperature, 59 to 86° F (15 to 30° C). Protect from moisture.
- Keep RITALIN-SR® and all medicines out of the reach of children.

General information about RITALIN-SR®

Medicines are sometimes prescribed for purposes other than those listed in a Medication Guide. Do not use RITALIN-SR® for a condition for which it was not prescribed. Do not give RITALIN-SR® to other people, even if they have the same condition. It may harm them and it is against the law.

This Medication Guide summarizes the most important information about RITALIN-SR®. If you would like more information, talk with your doctor. You can ask your doctor or pharmacist for information about RITALIN-SR® that was written for healthcare professionals. For more information about RITALIN-SR call 1-888-669-6682.

What are the ingredients in RITALIN-SR®?

Active Ingredient: methylphenidate HCL, USP

Inactive Ingredients: cellulose compounds, cetostearyl alcohol, lactose, magnesium stearate, mineral oil, povidone, titanium dioxide, and zein

Call your doctor for medical advice about side effects. You may report side effects to FDA at 1-800-FDA-1088.

This Medication Guide has been approved by the U.S. Food and Drug Administration.

REV: DECEMBER 2010 T2010-119/T2009-57/T2009-58

Novartis Pharmaceuticals Corporation

East Hanover, New Jersey 07936

© Novartis

Relabeling and Repackaging by:
Physicians Total Care, Inc.
Tulsa, Oklahoma 74146

PRINCIPAL DISPLAY PANEL

PACKAGE LABEL – 5 MG

Rx Only

Ritalin® HCL

Methylphenidate HCL USP

5 mg

Dispense with Medication Guide attached or provided separately.

PACKAGE LABEL – 20 MG

Rx Only

Ritalin® HCL

Methylphenidate HCL USP

20 mg

Dispense with Medication Guide attached or provided separately.